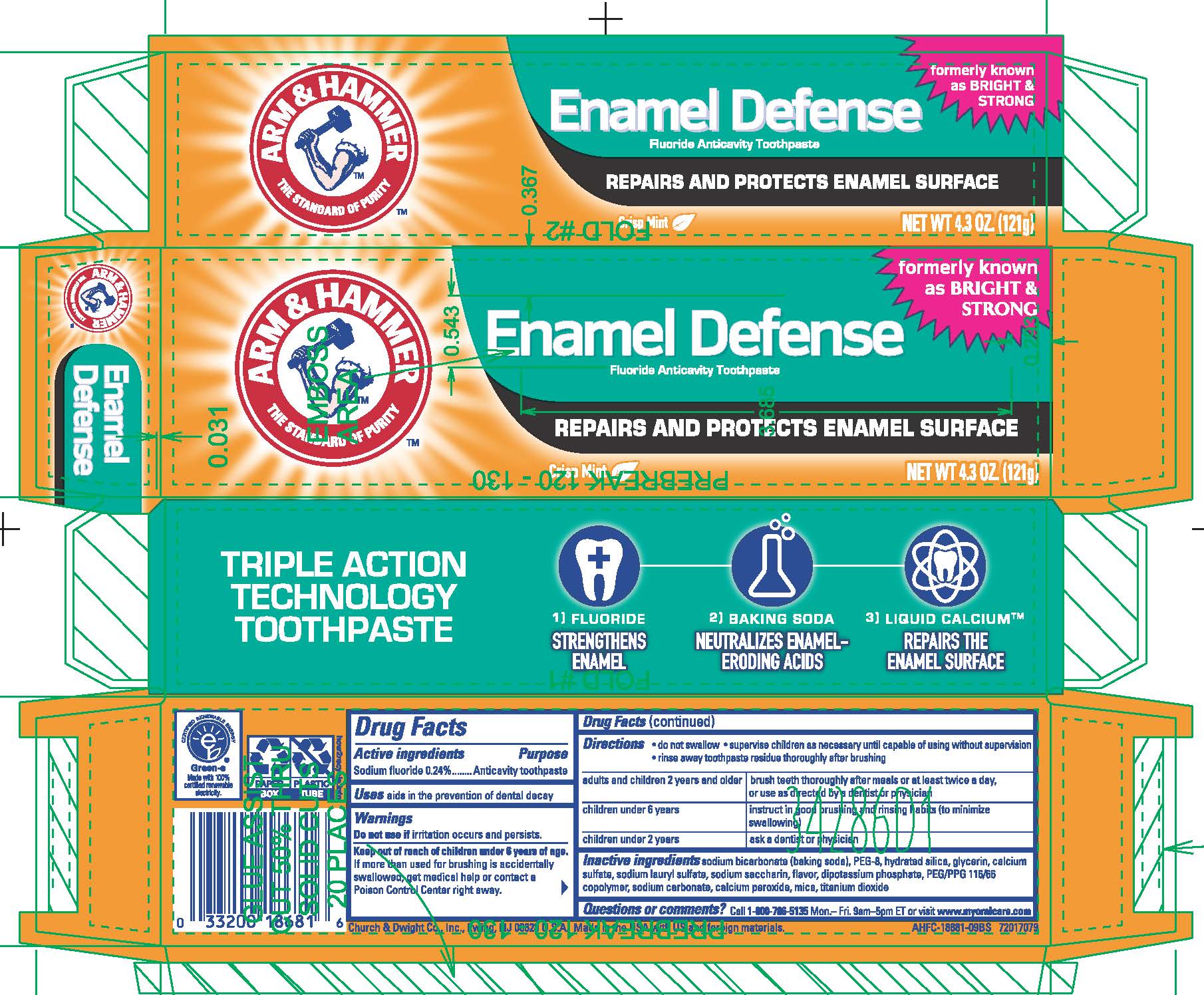 DRUG LABEL: Enamel Defense
NDC: 10237-666 | Form: PASTE, DENTIFRICE
Manufacturer: Church & Dwight Co., Inc.
Category: otc | Type: HUMAN OTC DRUG LABEL
Date: 20241120

ACTIVE INGREDIENTS: SODIUM FLUORIDE 0.24 mg/1 g
INACTIVE INGREDIENTS: METHYL SALICYLATE; MICA; POLYETHYLENE GLYCOL 400; SODIUM LAURYL SULFATE; GLYCERIN; SODIUM BICARBONATE; HYDRATED SILICA; CALCIUM SULFATE, UNSPECIFIED FORM; SACCHARIN SODIUM; DIBASIC POTASSIUM PHOSPHATE; PEG/PPG-116/66 COPOLYMER; SODIUM CARBONATE; CALCIUM PEROXIDE; TITANIUM DIOXIDE

ARM & HAMMER Enamel Defense Fluoride Anticavity Toothpaste

ACTIVE INGREDIENT

Sodium Fluoride 0.24%

PURPOSE

Anticavity toothpaste

Use

aids in the prevention of dental decay

Warnings

Do not use ifirritation occurs and persists.

Keep out of reach of children under 6 years of age.

If more than used for brushing is accidently swallowed, get medical help or contact a Poison Control Center right away.

Directions

- do not swallow
- supervise children as necessary until capable of using without supervision
- rinse away toothpaste residue thoroughly after brushing

adults and children 2 years and older- brush teeth thoroughly after meals or at least twice a day, or use as directed by a dentist or physician

children under 6 years- instruct in good brushing and rinsing habits (to minimize swallowing)

children under 2 years- ask a dentist or physician

INACTIVE INGREDIENT

sodium bicarbonate (baking soda), PEG-8, hydrated silica, glycerin, calcium sulfate, sodium lauryl sulfate, sodium saccharin, flavor, dipotassium phosphate, PEG/PPG 116/66 copolymer, sodium carbonate, calcium peroxide, mica, titanium dioxide

Questions or comments? Call 1-800-786-5135 Mon.-Fri. 9am-5pm ET or visit www.myoralcare.com

PACKAGE LABEL

ARM & HAMMER

THE STANDARD OF PURITY

Enamel Defense

Fluoride Anticavity Toothpaste

formerly known as BRIGHT & STRONG

REPAIRS AND PROTECTS ENAMEL SURFACE

Crisp Mint

NET WT 4.3 OZ. (121g)